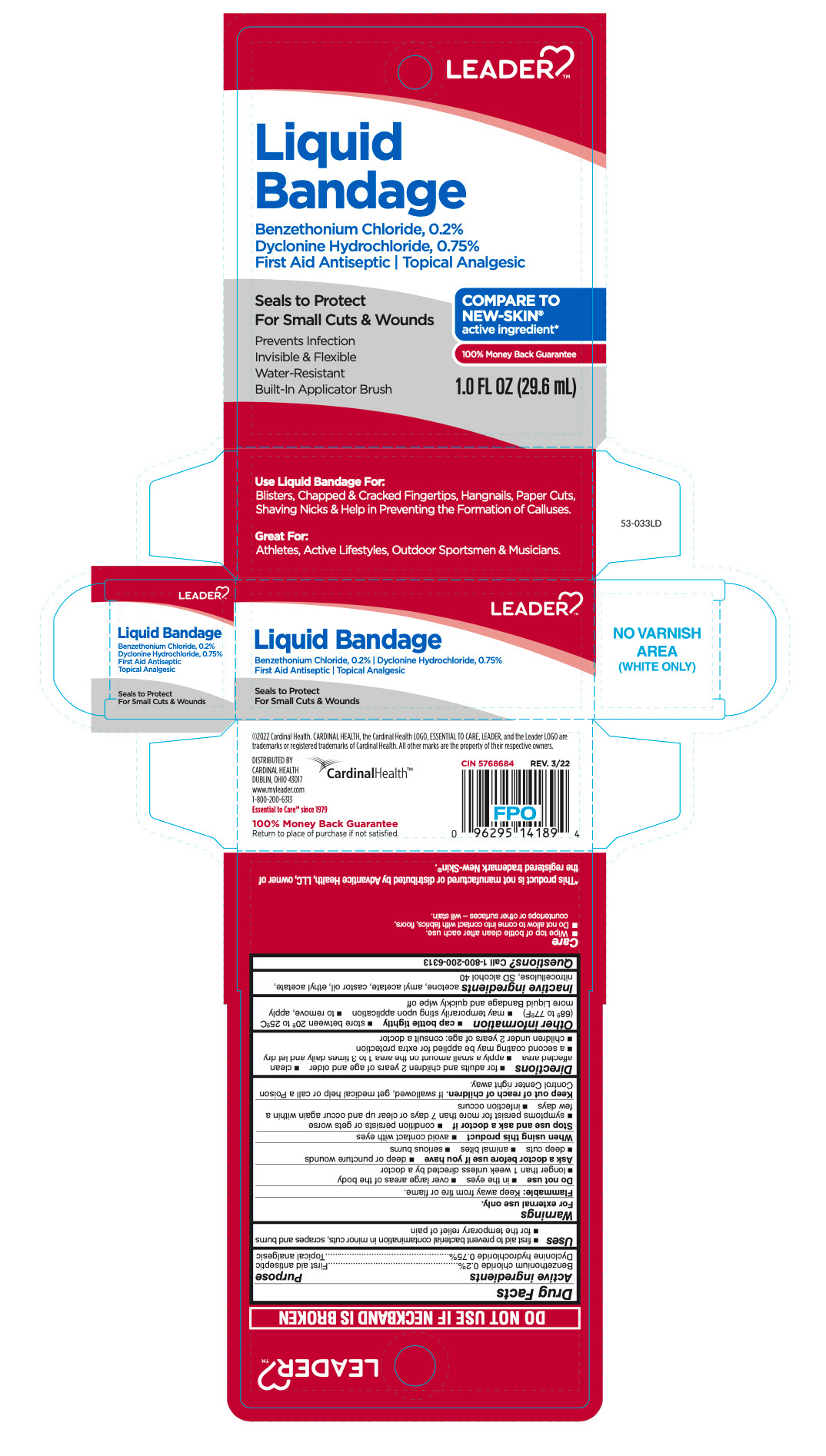 DRUG LABEL: Leader Liquid Bandage
NDC: 70000-0599 | Form: LIQUID
Manufacturer: LEADER/ Cardinal Health 110, Inc.
Category: otc | Type: HUMAN OTC DRUG LABEL
Date: 20251231

ACTIVE INGREDIENTS: BENZETHONIUM CHLORIDE 0.2 mg/10 mL; DYCLONINE HYDROCHLORIDE 0.75 mg/10 mL
INACTIVE INGREDIENTS: ACETONE; AMYL ACETATE; CASTOR OIL; ETHYL ACETATE; PYROXYLIN; ALCOHOL

Leader Liquid Bandage

Active ingredients

Benzethonium chloride 0.2%
Dyclonine hydrochloride 0.75%

Purpose

First aid antiseptic
Topical analgesic

Uses

- first aid to prevent bacterial contamination in minor cuts, scrapes and burns
- for the temporary relief of pain

Warnings

For external use only.

Flammable:

Keep away from fire or flame.

Do not use

- in the eyes
- over large areas of the body
- longer than 1 week unless directed by a doctor

Ask a doctor before use if you have

- deep puncture wounds
- deep cuts
- animal bites
- serious burns

When using this product

- avoid contact with eyes

Stop use and ask a doctor if

- condition persists or gets worse
- symptoms persist for more than 7 days or clear up and occur again within a few days
- infection occurs

Keep out of reach of children.

If swallowed, get medical help or call a Poison Control Center right away.

Directions

- for adults and children 2 years of age and older
- clean affected area
- apply a small amount on the area 1-3 times daily and let dry
- a second coating may be applied for extra protection
- children under 2 years of age: consult a doctor

Other information

- cap bottle tightly
- store between 20° to 25°C (68° to 77°F)
- may temporarily sting upon application
- to remove, apply more Liquid Bandage and quickly wipe off

Inactive ingredients

acetone, amyl acetate, castor oil, ethyl acetate, nitrocellulose, SD alcohol 40

Questions

Call 1-866-964-0939

Principal Display Panel

LEADER

Liquid

Bandage

Benzethonium Chloride, 0.2%
First Aid Antiseptic

Dyclonine Hydrochloride, 0.75%
Topical Analgesic

Seals to Protect
For Small Cuts & Wounds

Prevents Infection

Invisible & Flexible

Water-Resistant

Built-In Applicator Brush

1.0 FL OZ (29.6 mL)